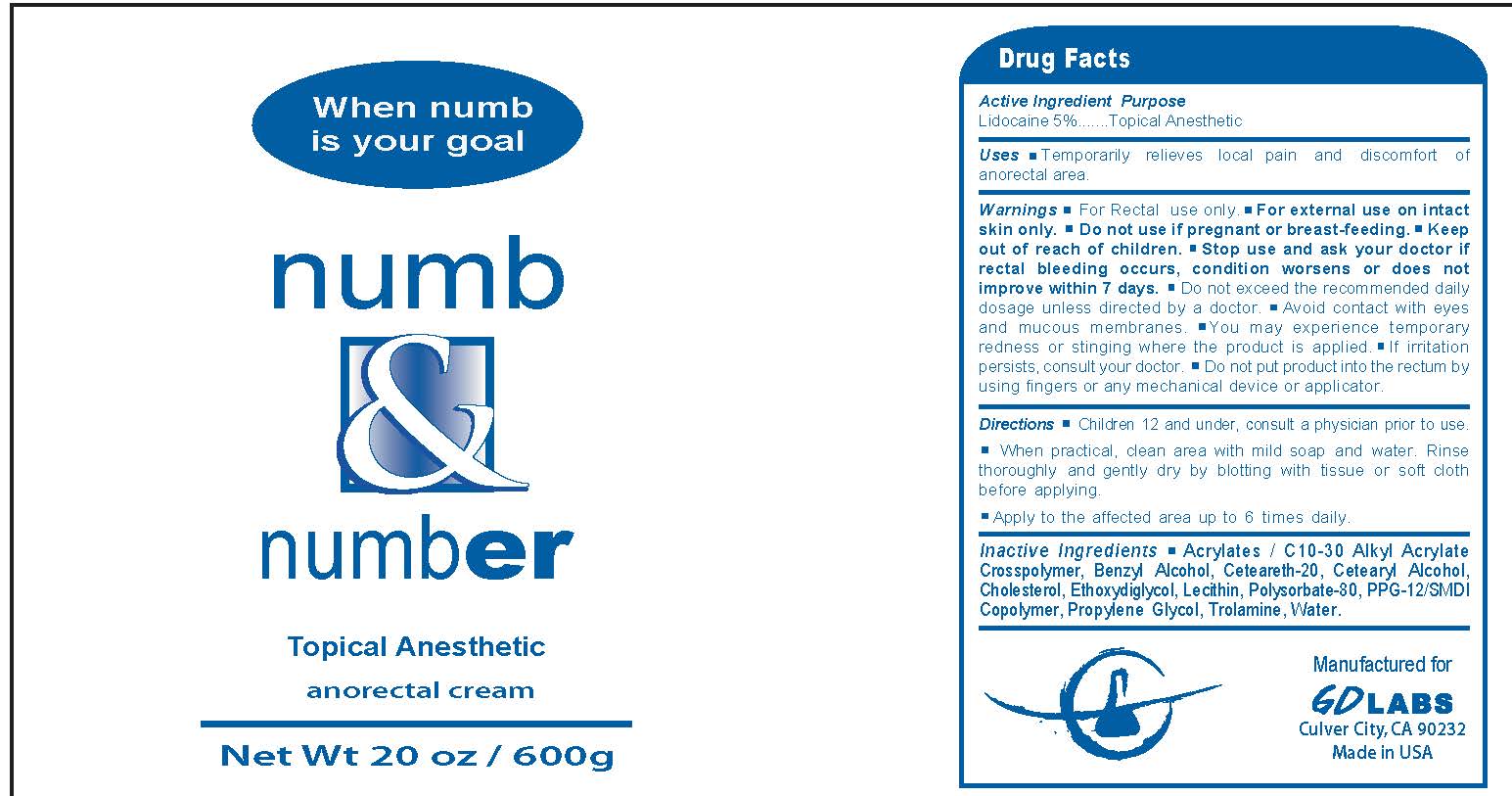 DRUG LABEL: Topical Anesthetic Anorectal Cream
NDC: 68848-001 | Form: CREAM
Manufacturer: Dermtech Labs Inc. dba GD Labs
Category: otc | Type: HUMAN OTC DRUG LABEL
Date: 20170103

ACTIVE INGREDIENTS: LIDOCAINE 5 g/100 g
INACTIVE INGREDIENTS: CARBOMER INTERPOLYMER TYPE A (ALLYL SUCROSE CROSSLINKED); BENZYL ALCOHOL; POLYOXYL 20 CETOSTEARYL ETHER; CETOSTEARYL ALCOHOL; CHOLESTEROL; DIETHYLENE GLYCOL MONOETHYL ETHER; HYDROGENATED SOYBEAN LECITHIN; POLYSORBATE 80; PPG-12/SMDI COPOLYMER; PROPYLENE GLYCOL; TROLAMINE; WATER

Numb & Number - Topical Anesthetic anorectal cream

Active Ingredient Purpose
Lidocaine 5% ..... Topical Anesthetic

PURPOSE

Temporarily relieves local pain and discomfort of anorectal area.

Keep out of reach of Chilren

Stop use and ask your doctor if rectal bleeding occurs, condition worsens or does not improve within 7 days.

WARNINGS

- For Rectal use only
- For external use on intact skin only
- Do not use if pregnant or breast-feeding
- Do not exceed the recommended daily dosage unless directded by a doctor
- Avoid contact with eyes and mucous membranes
- You may experience temporary redness or stinging where the product is applied
- If irritation persists, consult your doctor
- Do not put product into the rectum by using fingers or any mechanical device or applicator

DOSAGE AND ADMINISTRATION

- Children 12 and under, consult a physician prior to use
- When practical, clean area with mild soap and water. Rinse thoroughly and gently dry by blotting with tissue or soft cloth before applying.
- Apply to the affected area up to 6 times daily

INACTIVE INGREDIENT

Acrylates/C10-30 Alkyl Acrylate Crosspolymer, Benzyl Alcohol, Ceteareth-20, Cetearyl Alcohol, Cholesterol, Ethoxydiglycol, Lecithin, Polysorbate-80, PPG-12/SMDI Copolyme, Propylene Glycol, Trolamine, Water

PACKAGE LABEL

Numb & Number

Topical Anesthetic

Anorectal Cream

Net Wt 20 oz / 600g